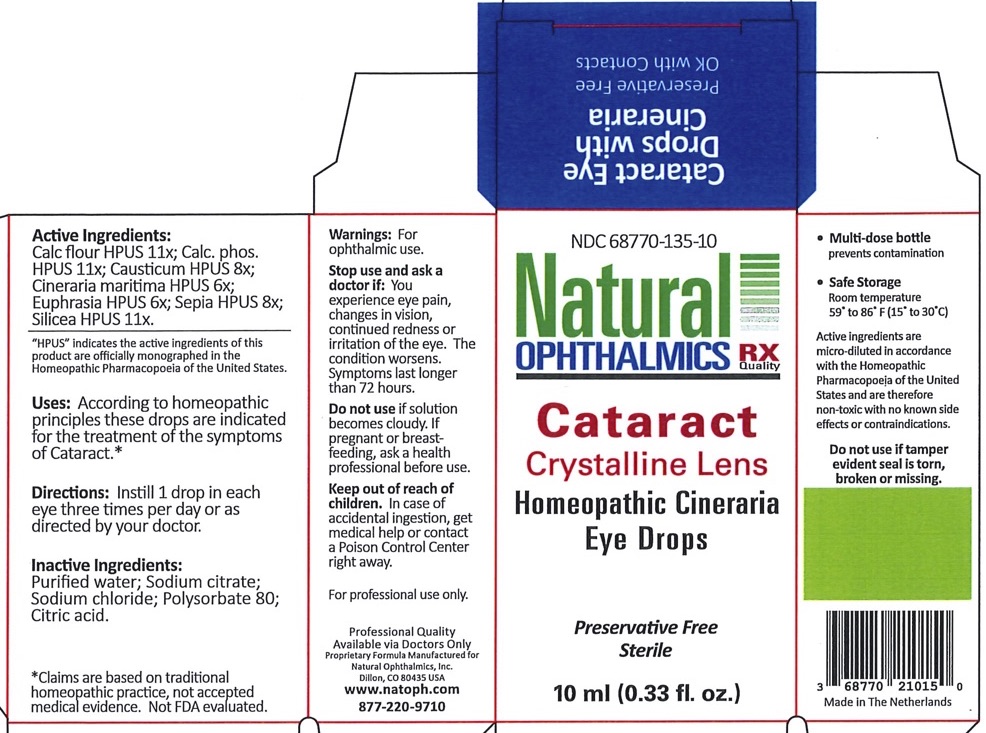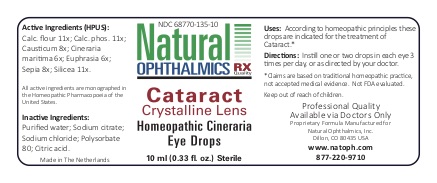 DRUG LABEL: Cataract Crystalline Lens
NDC: 68770-135 | Form: LIQUID
Manufacturer: Natural Ophthalmics, Inc
Category: homeopathic | Type: HUMAN OTC DRUG LABEL
Date: 20200714

ACTIVE INGREDIENTS: JACOBAEA MARITIMA 6 [hp_X]/1 mL; EUPHRASIA STRICTA 6 [hp_X]/1 mL; CAUSTICUM 8 [hp_X]/1 mL; TRIBASIC CALCIUM PHOSPHATE 11 [hp_X]/1 mL; SEPIA OFFICINALIS JUICE 8 [hp_X]/1 mL; CALCIUM FLUORIDE 11 [hp_X]/1 mL; SILICON DIOXIDE 11 [hp_X]/1 mL
INACTIVE INGREDIENTS: WATER; CITRIC ACID MONOHYDRATE; POLYSORBATE 80; SODIUM CHLORIDE

Cataract Crystalline Lens

Homeopathic Purpose

Cineraria Maritima HPUS | 6X | Increases circulation in the intraocular tissues
Euphrasia (Eyebright) HPUS | 6X | General dryness, redness and irritation of the eye and lids
Causticum HPUS | 8X | Eye pain
Calcarea phosphorica HPUS | 11X | Blurry vision, eye pain from reading
Sepia HPUS | 8X | Glares, black spots, veils, points, sparks, flashes and streaks of light
Calcarea fluorica HPUS | 11X | Cataract, corneal opacities, keratitis, flickering and floaters
Silicea HPUS | 11X | Spotted vision, cataract, opacities, keratitis

*Claims are based on traditional homeopathic practice, not accepted medicalevidence. Not FDA evaluated

Active Ingredients

Cineraria Maritima HPUS | 6X
Euphrasia (Eyebright) HPUS | 6X
Causticum HPUS | 8X
Calcarea phosphorica HPUS | 11X
Sepia HPUS | 8X
Calcarea fluorica HPUS | 11X
Silicea HPUS | 11X

"HPUS" indicates the active ingredients of this product are officially monographed in the Homeopathic Pharmacopoeia of the United States.

Inactive Ingredients

Purified water

Sodium chloride

Sodium citrate

Polysorbate 80

Citric acid

Uses

According to homeopathic principles these drops are indicated for the treatment of the symptoms of Cataract.*

*Claims are based on traditional homeopathic practice, not accepted medical evidence. Not FDA evaluated.

Directions

Instill 1drop in each eye three times per day or as directed by your doctor.

Warnings

- For ophthalmic use.
For professional use only.

Do not use if tamper evident seal is torn, broken. or missing.

Keep out of reach of children. In case of accidental ingestion, get medical help or contact a Poison Control Center right away.

If pregnant or breast feeding, ask a health professional before use.

Stop use and ask a doctor if: You experience eye pain, changes in vision, continued redness or irritation of the eye. The condition worsens. Symptoms last longer than 72 hours.

Do not use if solution becomes cloudy.

Storage

- Safe Storage

Room temperature
59o to 86o (15o to 30o C)

QUESTIONS

Natural Ophthalmics, Inc
Dillon, CO, 80435
1-877-220-9710
www.natoph.com